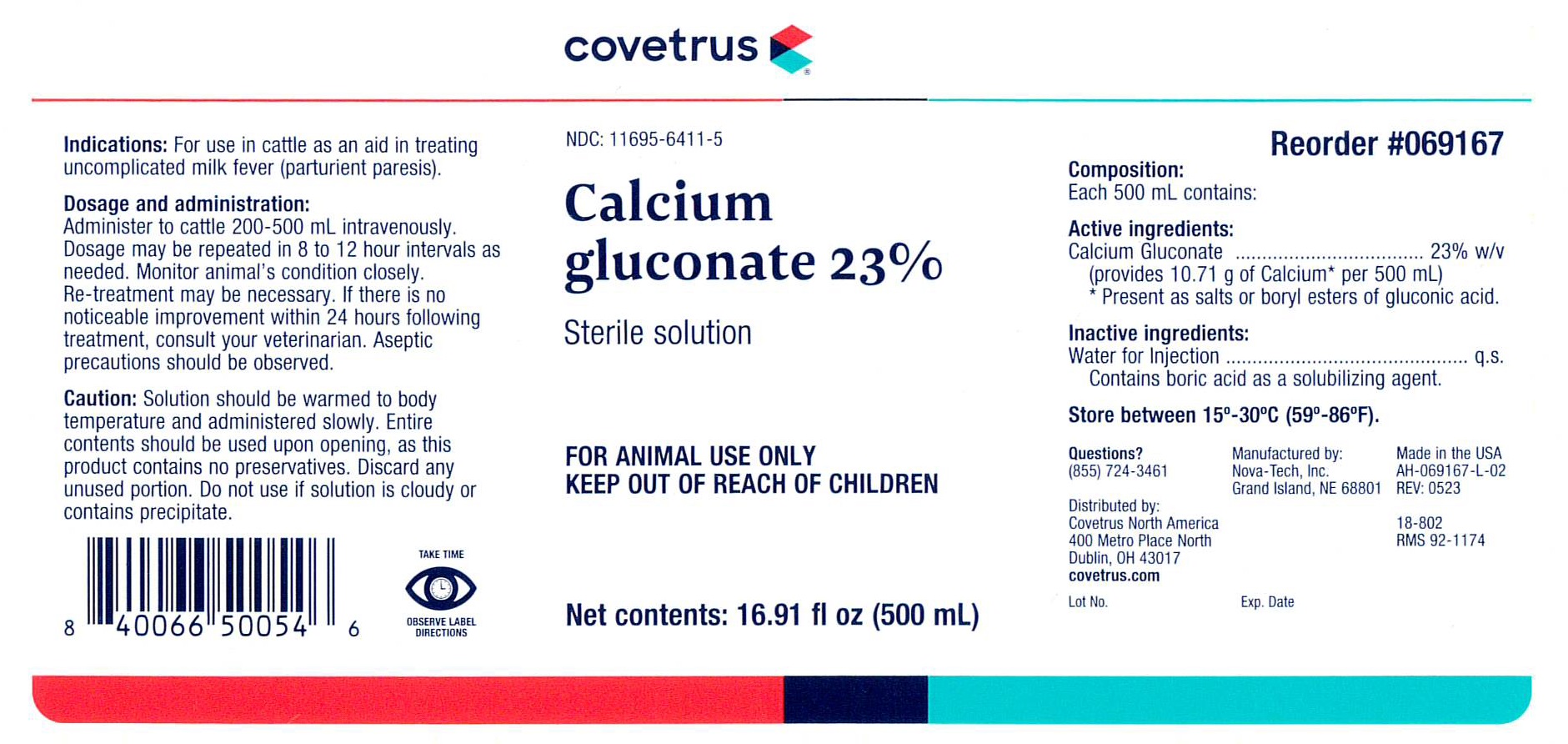 DRUG LABEL: Calcium Gluconate
NDC: 11695-6411 | Form: INJECTION, SOLUTION
Manufacturer: Covetrus
Category: animal | Type: OTC ANIMAL DRUG LABEL
Date: 20240405

ACTIVE INGREDIENTS: CALCIUM GLUCONATE 23 g/100 mL

CALCIUM GLUCONATE 23%

INDICATIONS:

For use in cattle as an aid in treating uncomplicated milk fever (parturient paresi).

DOSAGE AND ADMINISTRATION:

Administer to cattle 200-500 mL intravenously. Dosage may be repeated in 8 to 12 hour intervals as needed. Monitor animal's condition closely. Re-treatment may be necessary. If there is no noticeable improvement within 24 hours following treatment, consult your veterinarian. Aseptic precautions should be observed.

PRECAUTIONS

TAKE TIME OBSERVE LABEL DIRECTIONS

INFORMATION FOR OWNERS/CAREGIVERS

NDC 11695-6411-5

Calcium gluconate 23%

Sterile Solution

Net Contents: 16.91 fl oz (500 mL)

Questions? (855) 724-3461

Reorder #069167

18-802

RMS 92-1174

Made in the USA

AH-069167-L-02

REV: 0523

Lot No.

Exp. Date

Distributed by:

Covetrus North America

400 Metro Place North

Dublin, OH 43017

covetrus.com

Manufactured by:

Nova-Tech, Inc.

Grand Island, NE 68801

Composition:

Each 500 mL contains:

Active ingredients:

Calcium Gluconate ............................................ 23% w/v

(provides 10.71 g of Calcium* per 500 mL)

* Present as salts or boryl esters of gluconic acid.

Inactive ingredients:

Water for injection .................................. q.s.

Contains boric acid as a solubilizing agent.

STORAGE AND HANDLING

Store between 15°-30°C (59°-86°F).

GENERAL PRECAUTIONS

FOR ANIMAL USE ONLY

KEEP OUT OF REACH OF CHILDREN

Caution:

Solution should be warmed to body temperature and administered slowly. Entire contents should be used upon opening, as this product contains no preservatives. Discard any unused portion. Do not use if solution is cloudy or contains precipitate.